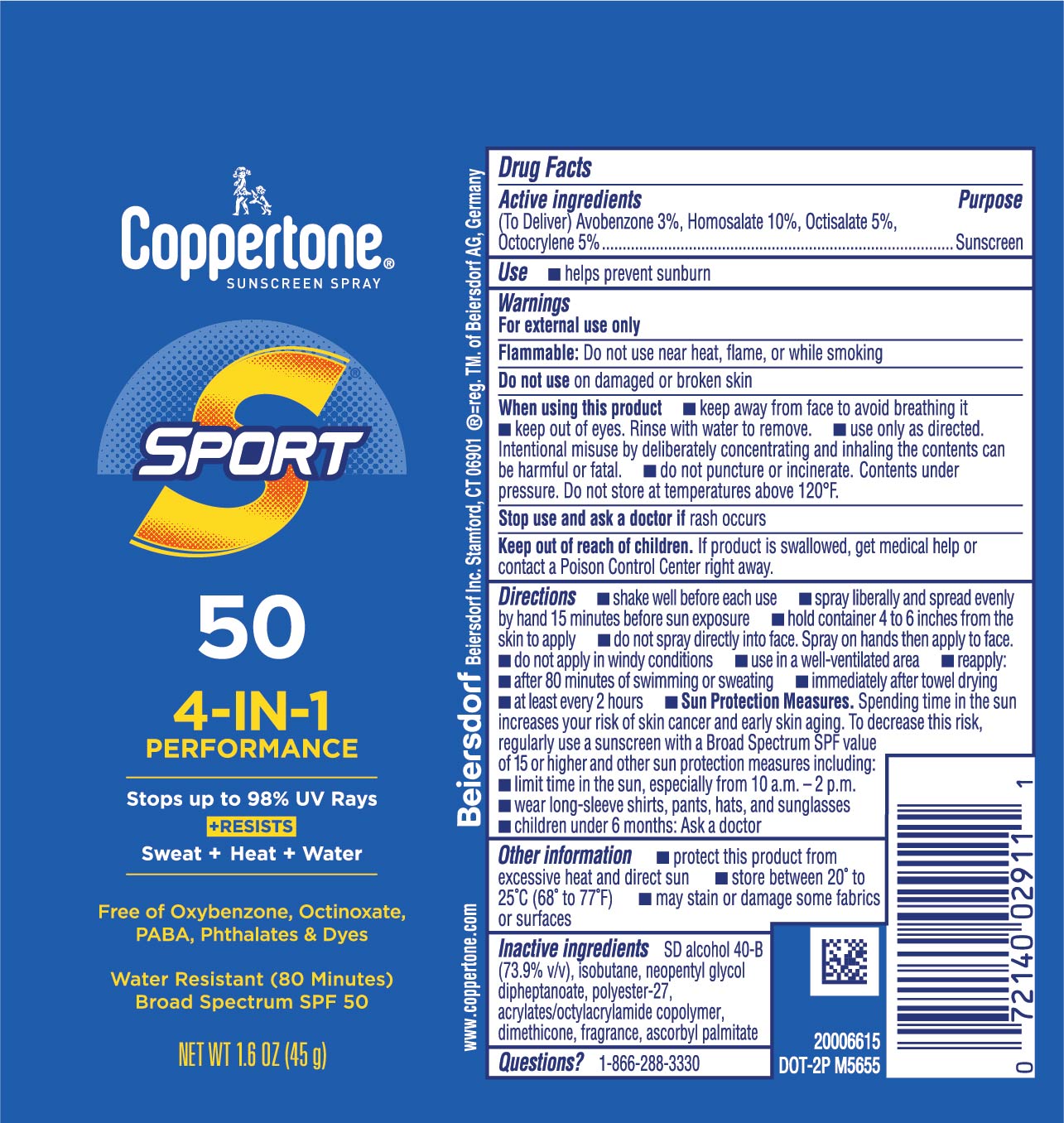 DRUG LABEL: Coppertone Sport Suncreen SPF 50
NDC: 66800-4356 | Form: AEROSOL, SPRAY
Manufacturer: Beiersdorf Inc
Category: otc | Type: HUMAN OTC DRUG LABEL
Date: 20251231

ACTIVE INGREDIENTS: HOMOSALATE 10 g/100 g; OCTOCRYLENE 5 g/100 g; OCTISALATE 5 g/100 g; AVOBENZONE 3 g/100 g
INACTIVE INGREDIENTS: ALCOHOL; NEOPENTYL GLYCOL DIHEPTANOATE; ASCORBYL PALMITATE; ISOBUTANE; POLYESTER-7; FRAGRANCE FLORAL ORC0902236; ACRYLATE/ISOBUTYL METHACRYLATE/N-TERT-OCTYLACRYLAMIDE COPOLYMER (75000 MW); DIMETHICONE

Sport Spray SPF 50

Active ingredients

Avobenzone 3%, Homosalate 10%, Octisalate 5%, Octocrylene 5%

Purpose

Sunscreen

Use

■ helps prevent sunburn

Warnings

For external use only

Flammable: Do not use near heat, flame, or while smoking

Do not useon damaged or broken skin

When using this product
■ keep away from face to avoid breathing it

■ keep out of eyes. Rinse with water to remove.

■ use only as directed. Intentional misuse by deliberately concentrating and inhaling the contents can be harmful or fatal.

■ do not puncture or incinerate. Contents under pressure. Do not store at temperatures above 120˚F.

Stop use and ask a doctor ifrash occurs

Keep out of reach of children.If product is swallowed, get medical help or contact a Poison Control Center right away.

Directions

■ shake well before each use

■ spray liberally and spread evenly by hand 15 minutes before sun exposure

■ hold container 4 to 6 inches from the skin to apply

■ do not spray directly into face. Spray on hands then apply to face.

■ do not apply in windy conditions

■ use in a well-ventilated area

■ reapply:

■ after 80 minutes of swimming or sweating

■ immediately after towel drying

■ at least every 2 hours

■ Sun Protection Measures. Spending time in the sun increases your risk of skin cancer and early skin aging. To decrease this risk, regularly use a sunscreen with a Broad Spectrum SPF value of 15 or higher and other sun protection measures including:

■ limit time in the sun, especially from 10 a.m. – 2 p.m.

■ wear long-sleeve shirts, pants, hats, and sunglasses

■ children under 6 months: Ask a doctor

Other information

■ protect this product from excessive heat and direct sun

■ store between 20˚ to 25˚C (68˚ to 77˚F)

■ may stain or damage some fabrics or surfaces

Inactive ingredients

SD alcohol 40-B (73.9% v/v), isobutane, neopentyl glycol dipheptanoate, polyester-27, acrylates/octylacrylamide copolymer, dimethicone, fragrance, ascorbyl palmitate

Questions

1-866-288-3330

PACKAGE LABEL

Coppertone®Sunscreen Spray

Sport

50

4-in-1 Performance

Stops up to 98% UV Rays

+ Resists Sweat + Heat + Water

Free of Oxybenzone, Octinoxate, PABA & Dyes

Water Resistant (80 Minutes)

Broad Spectrum SPF 50

NET WT 1.6 OZ (45 g)